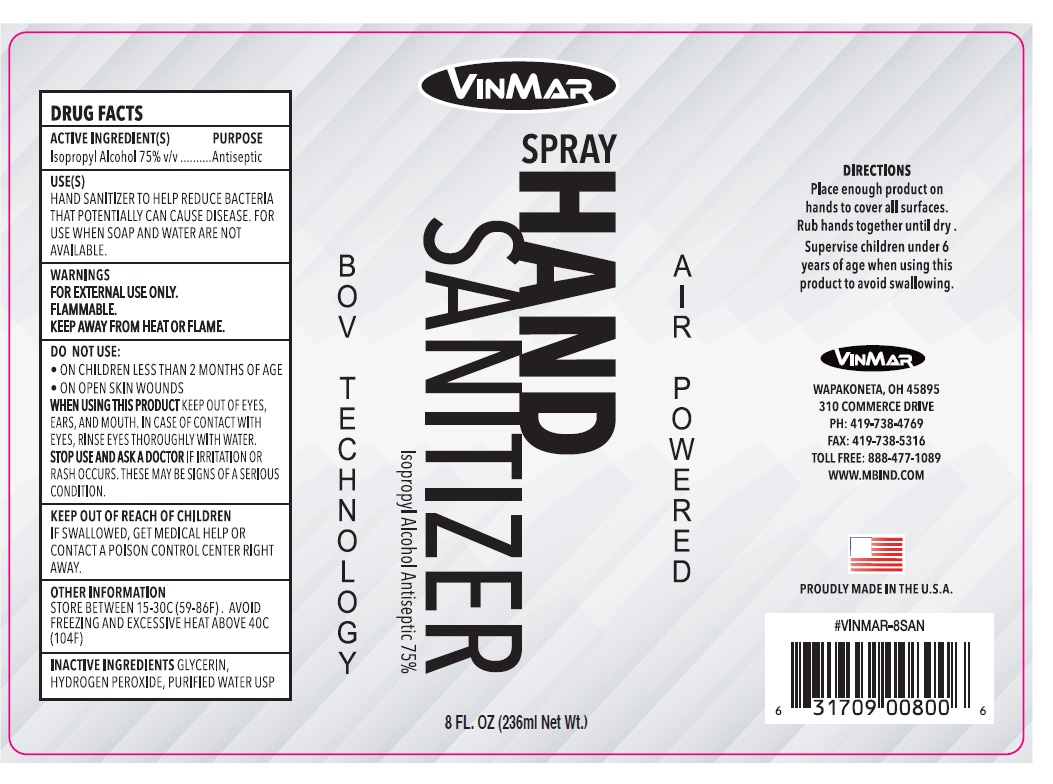 DRUG LABEL: VINMAR HAND SANITIZER
NDC: 77789-513 | Form: SPRAY
Manufacturer: Vin Mar Industries LLC
Category: otc | Type: HUMAN OTC DRUG LABEL
Date: 20200515

ACTIVE INGREDIENTS: ISOPROPYL ALCOHOL 75 mL/100 mL
INACTIVE INGREDIENTS: GLYCERIN; HYDROGEN PEROXIDE; WATER

VINMAR HAND SANITIZER

ACTIVE INGREDIENT(S)

Isopropyl Alcohol 75% v/v

PURPOSE

Antiseptic

USE(S)

HAND SANITIZER TO HELP REDUCE BACTERIA THAT POTENTIALLY CAN CAUSE DISEASE. FOR USE WHEN SOAP AND WATER ARE NOT AVAILABLE.

WARNINGS

FOR EXTERNAL USE ONLY.

FLAMMABLE.

KEEP AWAY FROM HEAT OR FLAME.

DO NOT USE:

- ON CHILDREN LESS THAN 2 MONTHS OF AGE
- ON OPEN SKIN WOUNDS

WHEN USING THIS PRODUCT KEEP OUT OF EYES, EARS, AND MOUTH. IN CASE OF CONTACT WITH EYES, RINSE EYES THOROUGHLY WITH WATER.

STOP USE AND ASK A DOCTOR IF IRRITATION OR RASH OCCURS. THESE MAY BE SIGNS OF A SERIOUS CONDITION.

KEEP OUT OF REACH OF CHILDREN. IF SWALLOWED, GET MEDICAL HELP OR CONTACT A POISON CONTROL CENTER RIGHT AWAY.

DIRECTIONS

Place enough product on hands to cover all surfaces. Rub hands together until dry. Supervise children under 6 years of age when using this product to avoid swallowing.

OTHER INFORMATION

STORE BETWEEN 15-30C (59-86F). AVOID FREEZING AND EXCESSIVE HEAT ABOVE 40C (104F)

INACTIVE INGREDIENTS

GLYCERIN, HYDROGEN PEROXIDE, PURIFIED WATER USP

AIR POWERED

BOV TECHNOLOGY

VINMAR

WAPAKONETA, OH 45895

310 COMMERCE DRIVE

PH: 419-738-4769

FAX: 419-738-5316

TOLL FREE: 888-477-1089

WWW.MBIND.COM

PROUDLY MADE IN THE U.S.A.